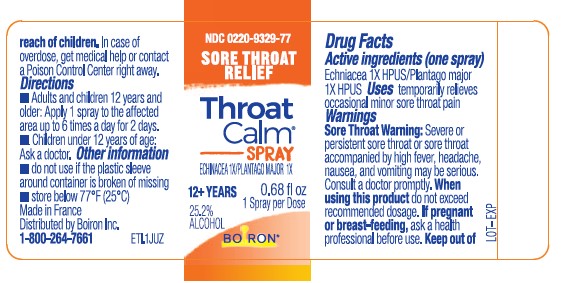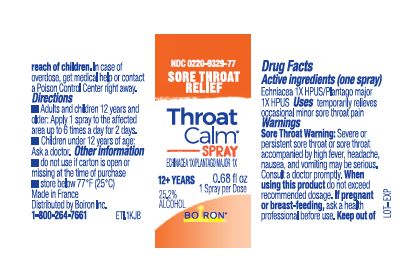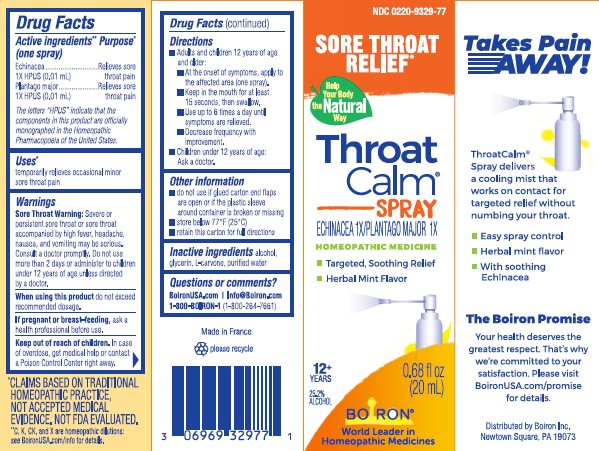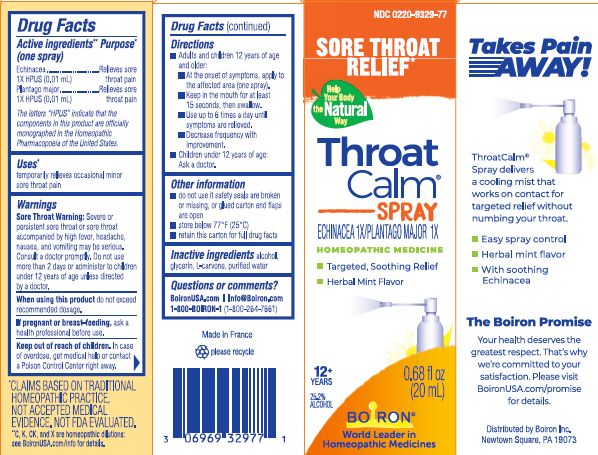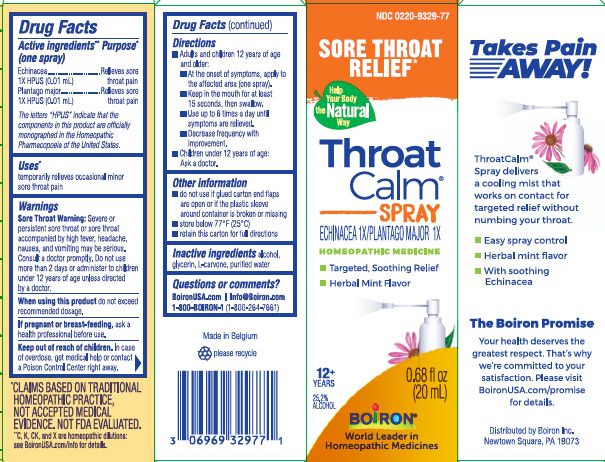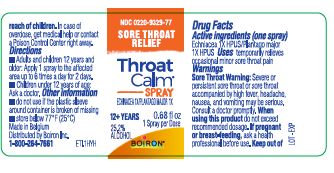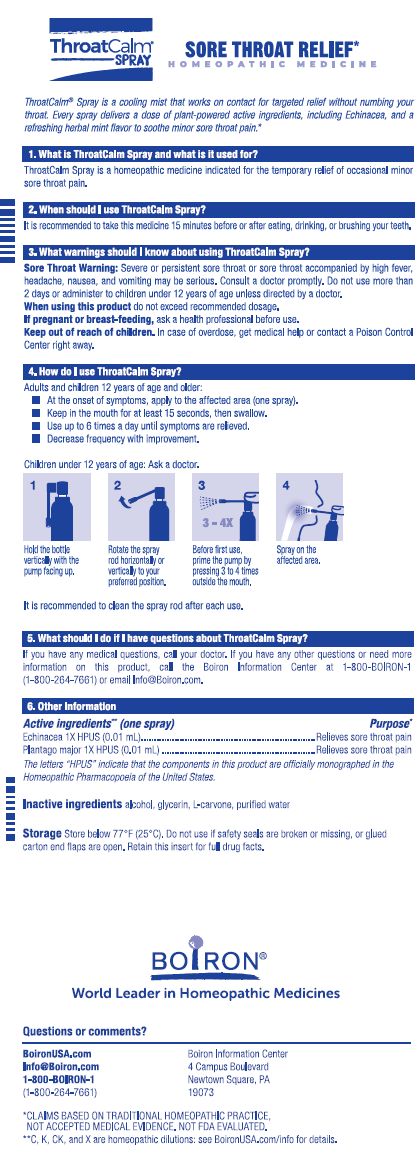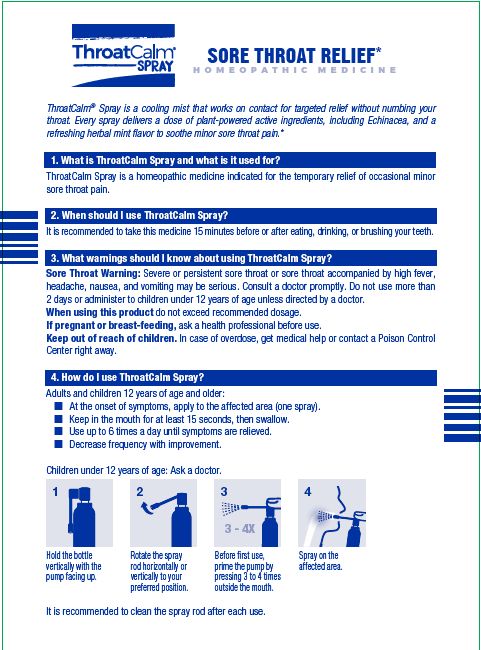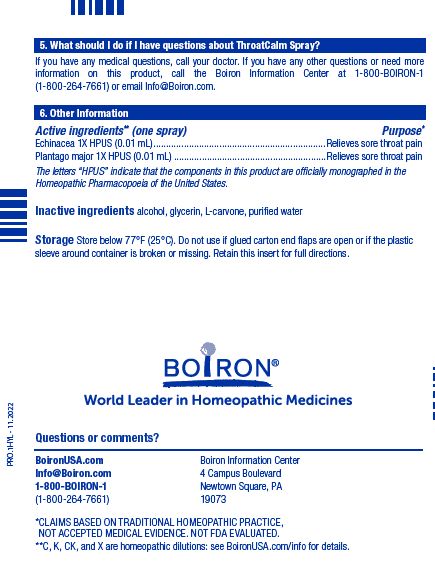 DRUG LABEL: THROATCALM
NDC: 0220-9329 | Form: SPRAY
Manufacturer: Boiron
Category: homeopathic | Type: HUMAN OTC DRUG LABEL
Date: 20241218

ACTIVE INGREDIENTS: ECHINACEA ANGUSTIFOLIA WHOLE 1 [hp_X]/1 mL; PLANTAGO MAJOR WHOLE 1 [hp_X]/1 mL
INACTIVE INGREDIENTS: CARVONE, (-)-; ALCOHOL; WATER; GLYCERIN

ThroatCalm Spray

Active ingredients** (one spray)

Echinacea 1X HPUS (0.01 mL)

Plantago major 1X HPUS (0.01 mL)

The letters "HPUS" indicate that the components in this product are officially monographed in the Homeopathic Pharmacopoeia of the United States.

Purpose*

Echinacea 1X HPUS (0.01 mL) ... Relieves sore throat pain

Plantago major 1X HPUS (0.01 mL) ... Relieves sore throat pain

Uses*

temporarily relieves occasional minor sore throat pain

WARNINGS

Sore Throat Warning: Severe or persistent throat or sore throat accompanied by high fever, headache, nausea, and vomiting may be serious. Consult a doctor promptly. Do not use more than 2 days or administer to children under 12 years of age unless directed by a doctor.

When using this product do not exceed recommended dosage.

PREGNANCY OR BREAST FEEDING

If pregnant or breast-feeding, ask a health professional before use.

Keep out of reach of children. In case of overdose, get medical help or contact a Poison Control Center right away.

Directions

- Adults and children 12 years of age and older:
- At the onset of symptoms, apply to the affected area (one spray).
- Keep in mouth for at least 15 seconds, then swallow.
- Use up to 6 times a day until symptoms are relieved.
- Decrease frequency with improvement.
- Children under 12 years of age: Ask a doctor.

INACTIVE INGREDIENT

alcohol, glycerin, L-carvone, purified water

Sore Throat Relief*

Targeted, Soothing Relief

Herbal Mint Flavor

do not use if safety seals are broken or missing, or glued carton end flaps are open

store below 77o F (25o C)

retain this carton for full directions

0.68 fl oz

(20 mL)

1 spray per dose
25.2% ALCOHOL

*CLAIMS BASED ON TRADITIONAL HOMEOPATHIC, NOT ACCEPTED MEDICAL EVIDENCE. NOT FDA EVALUATED.

**C, K, CK and X are homeopathic dilutions: see BoironUSA.com/info for details.

Questions or comments?

BoironUSA.com

Info@Boiron.com

1-800-BOIRON-1 (1-800-264-7661)

Distributed by Boiron, Inc.

Newtown Square, PA 19073

Made in France